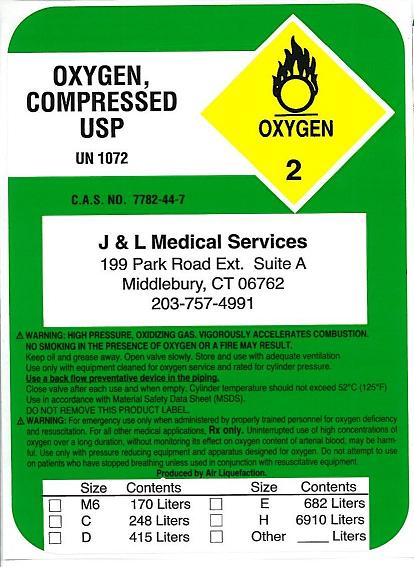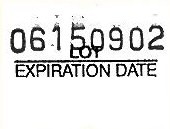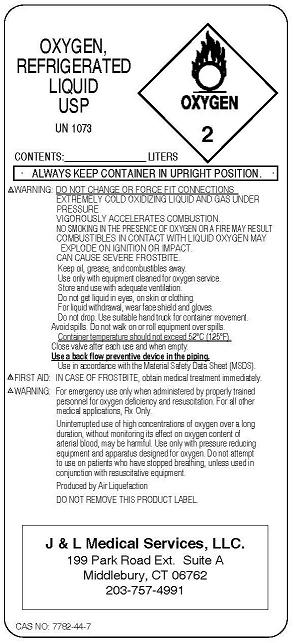 DRUG LABEL: Oxygen
NDC: 67750-1234 | Form: GAS
Manufacturer: J & L Medical Services LLC
Category: prescription | Type: HUMAN PRESCRIPTION DRUG LABEL
Date: 20091116

ACTIVE INGREDIENTS: Oxygen 99 L/100 L

Oxygen